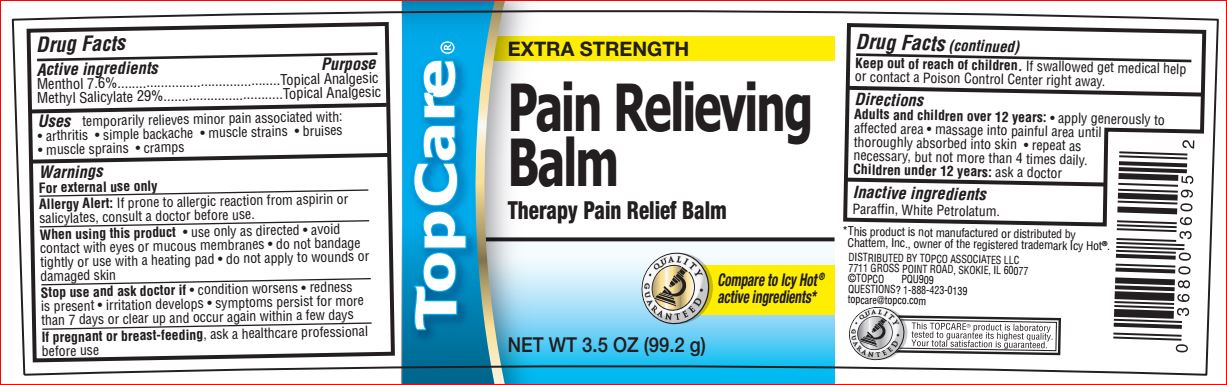 DRUG LABEL: Pain Relieving Balm
NDC: 36800-738 | Form: LIQUID
Manufacturer: TopCo
Category: otc | Type: HUMAN OTC DRUG LABEL
Date: 20180724

ACTIVE INGREDIENTS: Menthol 7.6 g/100 g; Methyl Salicylate 29 g/100 g
INACTIVE INGREDIENTS: Paraffin; PETROLATUM

Drug Facts

Active ingredients Purpose
Menthol 7.6%.............................................Topical Analgesic
Methyl Salicylate 29%.................................Topical Analgesic

Uses

temporarily relieves minor pain associated with:
• arthritis • simple backache • muscle strains • bruises
• muscle sprains • cramps

Warnings
For external use only
Allergy Alert: If prone to allergic reaction from aspirin or
salicylates, consult a doctor before use.
When using this product • use only as directed • avoid
contact with eyes or mucous membranes • do not bandage
tightly or use with a heating pad • do not apply to wounds or
damaged skin
Stop use and ask doctor if • condition worsens • redness
is present • irritation develops • symptoms persist for more
than 7 days or clear up and occur again within a few days
If pregnant or breast-feeding, ask a healthcare professional
before use

Keep out of reach of children.

If swallowed get medical help or contact a Poison Control Center right away.

Directions
Adults and children over 12 years: • apply generously to
affected area • massage into painful area until
thoroughly absorbed into skin • repeat as
necessary, but not more than 4 times daily.
Children under 12 years: ask a doctor

Inactive ingredients
Paraffin, White Petrolatum